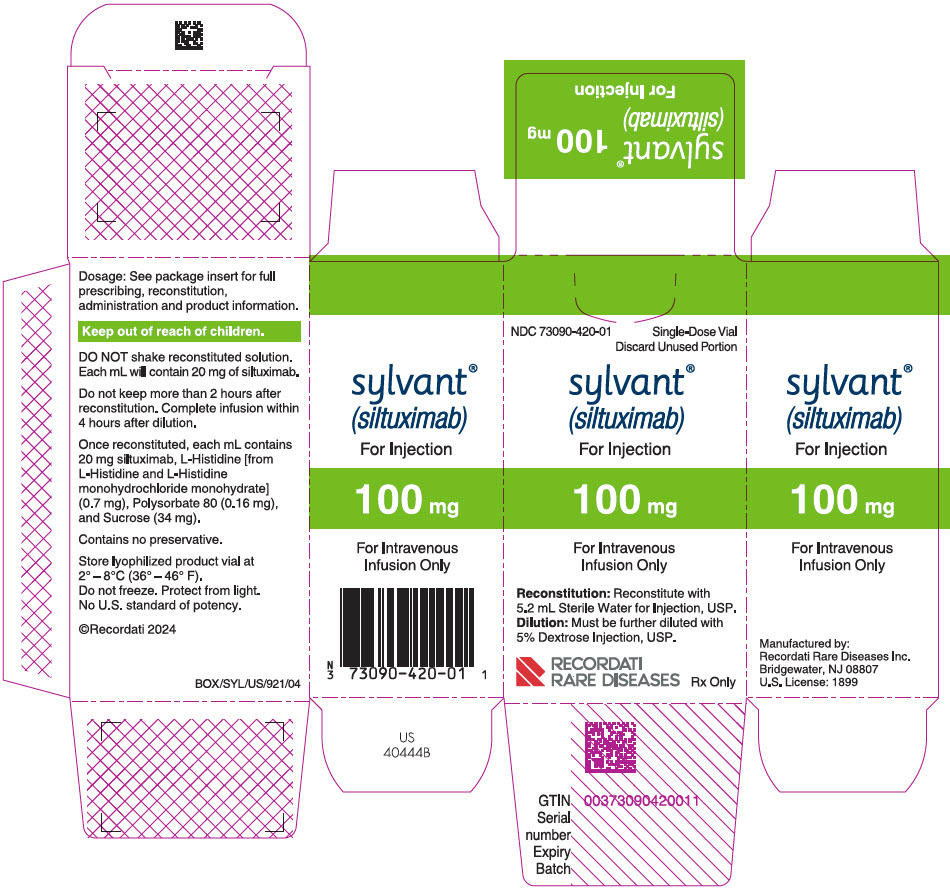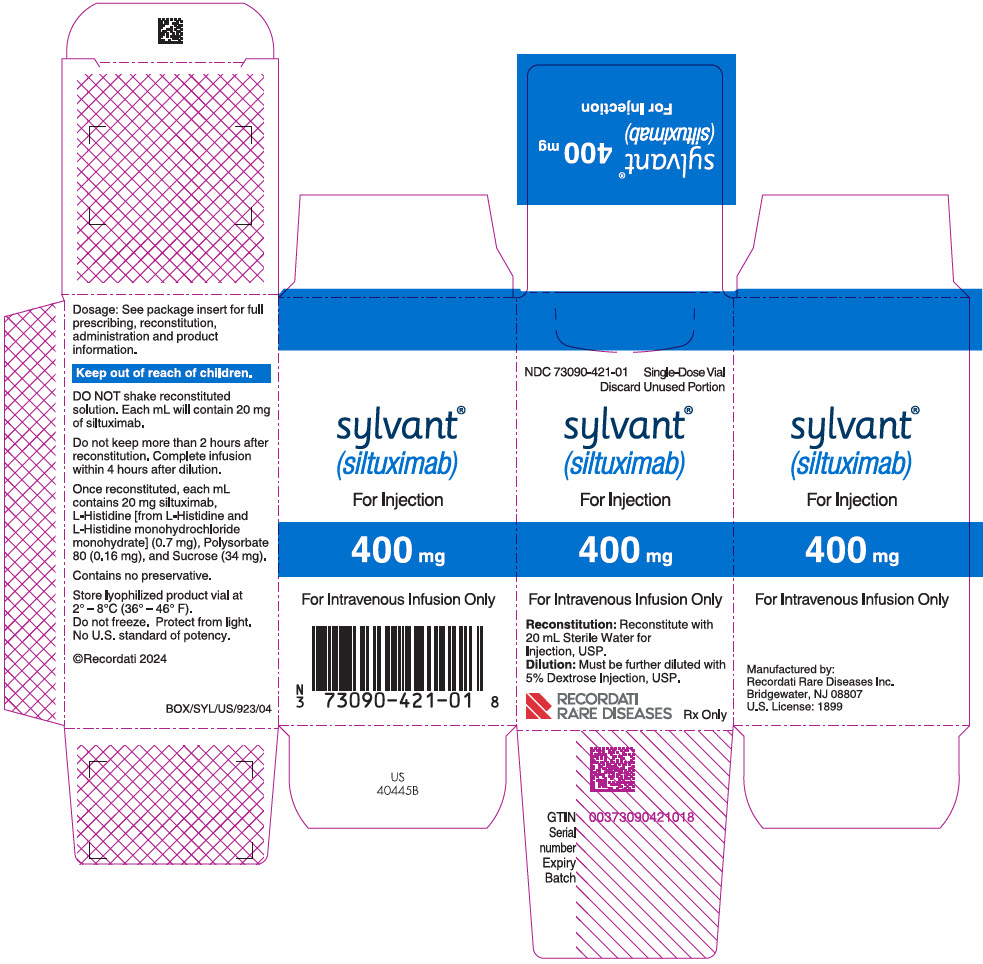 DRUG LABEL: Sylvant
NDC: 73090-420 | Form: INJECTION, POWDER, FOR SOLUTION
Manufacturer: Recordati Rare Diseases, Inc.
Category: prescription | Type: HUMAN PRESCRIPTION DRUG LABEL
Date: 20240827

ACTIVE INGREDIENTS: SILTUXIMAB 100 mg/1 1
INACTIVE INGREDIENTS: SUCROSE 169 mg/1 1; HISTIDINE; POLYSORBATE 80

HIGHLIGHTS OF PRESCRIBING INFORMATION

These highlights do not include all the information needed to use SYLVANT® safely and effectively. See full prescribing information for SYLVANT.
SYLVANT (siltuximab) for injection, for intravenous use
Initial U.S. Approval: 2014

1 INDICATIONS AND USAGE

SYLVANT is an interleukin-6 (IL-6) antagonist indicated for the treatment of patients with multicentric Castleman's disease (MCD) who are human immunodeficiency virus (HIV) negative and human herpesvirus-8 (HHV-8) negative. (1)

Limitations of Use

SYLVANT was not studied in patients with MCD who are HIV positive or HHV-8 positive because SYLVANT did not bind to virally produced IL-6 in a nonclinical study.

2 DOSAGE AND ADMINISTRATION

For intravenous infusion only.

Administer as an 11 mg/kg dose given over 1 hour by intravenous infusion every 3 weeks. (2)

3 DOSAGE FORMS AND STRENGTHS

For injection

- 100 mg of lyophilized powder in a single-dose vial. (3)
- 400 mg of lyophilized powder in a single-dose vial. (3)

4 CONTRAINDICATIONS

Severe hypersensitivity reaction to siltuximab or any of the excipients in SYLVANT. (4)

5 WARNINGS AND PRECAUTIONS

- Concurrent Active Severe Infections: Do not administer SYLVANT to patients with severe infections, monitor for infections, institute prompt treatment, and interrupt SYLVANT until resolution of infection. (2, 5.1)
- Vaccinations: Do not administer live vaccines because IL-6 inhibition may interfere with the normal immune response to new antigens. (5.2)
- Infusion Related Reactions: Administer SYLVANT in a setting that provides resuscitation equipment, medication, and personnel trained to provide resuscitation. (5.3, 6.1)
- Gastrointestinal (GI) perforation: Promptly evaluate patients presenting with symptoms that may be associated or suggestive of GI perforation. (5.4)

6 ADVERSE REACTIONS

The most common adverse reactions (>10% of patients) were rash, pruritus, upper respiratory tract infection, increased weight, and hyperuricemia.

To report SUSPECTED ADVERSE REACTIONS, contact Recordati Rare Diseases Inc., at 1-888-575-8344 or FDA at 1-800-FDA-1088 or www.fda.gov/medwatch.

8 USE IN SPECIFIC POPULATIONS

Pregnancy: May cause fetal harm (8.1)

FULL PRESCRIBING INFORMATION

1 INDICATIONS AND USAGE

SYLVANT is indicated for the treatment of patients with multicentric Castleman's disease (MCD) who are human immunodeficiency virus (HIV) negative and human herpesvirus-8 (HHV-8) negative.

Limitations of Use

SYLVANT was not studied in patients with MCD who are HIV positive or HHV-8 positive because SYLVANT did not bind to virally produced IL-6 in a nonclinical study.

2 DOSAGE AND ADMINISTRATION

2.1 Recommended Dosage

Administer SYLVANT 11 mg/kg over 1 hour as an intravenous infusion every 3 weeks until treatment failure.

Perform hematology laboratory tests prior to each dose of SYLVANT therapy for the first 12 months and every 3 dosing cycles thereafter. If treatment criteria outlined in Table 1 are not met, consider delaying treatment with SYLVANT. Do not reduce dose.

Table 1: Treatment Criteria
Laboratory parameter | Requirements before first SYLVANT administration | Retreatment criteria
Absolute Neutrophil Count | ≥1.0 × 10^9/L | ≥1.0 × 10^9/L
Platelet count | ≥75 × 10^9/L | ≥50 × 10^9/L
Hemoglobin [SYLVANT may increase hemoglobin levels in MCD patients] | <17 g/dL | <17 g/dL

Do not administer SYLVANT to patients with severe infections until the infection resolves.

Discontinue SYLVANT in patients with severe infusion related reactions, anaphylaxis, severe allergic reactions, or cytokine release syndromes. Do not reinstitute treatment.

2.2 Instructions for Preparation and Administration

Use aseptic technique for reconstitution and preparation of dosing solution.

Parenteral drug products should be inspected visually for particulate matter and discoloration prior to administration, whenever solution and container permit

1. Calculate the dose (mg), total volume (mL) of reconstituted SYLVANT solution required and the number of vials needed. A 21-gauge 1½ inch needle is recommended for preparation. Infusion bags (250 mL) must contain Dextrose 5% in Water and must be made of polyvinyl chloride (PVC), or polyolefin (PO), or polypropylene (PP), or polyethylene (PE). Alternatively PE bottles may be used.

2. Allow the vial(s) of SYLVANT to come to room temperature over approximately 30 minutes. SYLVANT should remain at room temperature for the duration of the preparation.

3. Aseptically reconstitute each SYLVANT vial as instructed in Table 2.

Table 2: Reconstitution Instructions
Strength | Amount of Sterile Water for Injection, USP required for reconstitution | Post-reconstitution concentration
100 mg vial | 5.2 mL | 20 mg/mL
400 mg vial | 20 mL | 20 mg/mL

Gently swirl the reconstituted vials to aid the dissolution of the lyophilized powder. DO NOT SHAKE or SWIRL VIGOROUSLY. Do not remove the contents until all of the solids have been completely dissolved. The lyophilized powder should dissolve in less than 60 minutes.

Once reconstituted, and prior to further dilution, inspect the vials for particulates and discoloration. Do not use if particles or solution discoloration are present or if visibly opaque. The reconstituted product should be kept for no more than two hours prior to addition into the infusion bag.

4. Dilute the reconstituted SYLVANT solution dose to 250 mL with sterile Dextrose 5% in Water by withdrawing a volume equal to the total calculated volume of reconstituted SYLVANT from the Dextrose 5% in Water, 250 mL bag. Slowly add the total calculated volume (mL) of reconstituted SYLVANT solution to the Dextrose 5% in Water infusion bag. Gently invert the bag to mix the solution.

5. Administer the diluted SYLVANT solution in 5% Dextrose in Water 250 mL by intravenous infusion over a period of 1 hour using administration sets lined with PVC, or polyurethane (PU), or PE, containing a 0.2-micron inline polyethersulfone (PES) filter. The infusion should be completed within 4 hours of the dilution of the reconstituted solution to the infusion bag.

6. Do not infuse SYLVANT concomitantly in the same intravenous line with other agents.

7. SYLVANT does not contain preservatives. Do not store any unused portion of the reconstituted product or of the infusion solution. Waste material should be disposed of in accordance with local requirements.

3 DOSAGE FORMS AND STRENGTHS

SYLVANT (siltuximab) for injection is available as:

- 100 mg of lyophilized powder in a single-dose vial for intravenous infusion.
- 400 mg of lyophilized powder in a single-dose vial for intravenous infusion.

4 CONTRAINDICATIONS

Severe hypersensitivity reaction to siltuximab or any of the excipients in SYLVANT [see Warnings and Precautions (5.3)]. Hypersensitivity reactions, including anaphylactic reaction, hypersensitivity, and drug hypersensitivity have been reported in patients treated with siltuximab.

5 WARNINGS AND PRECAUTIONS

5.1 Concurrent Active Severe Infections

Do not administer SYLVANT to patients with severe infections until the infection resolves. SYLVANT may mask signs and symptoms of acute inflammation including suppression of fever and of acute Phase reactants such as C-reactive protein (CRP). Monitor patients receiving SYLVANT closely for infections. Institute prompt anti-infective therapy and do not administer further SYLVANT until the infection resolves.

5.2 Vaccinations

Do not administer live vaccines to patients or infants born to patients receiving SYLVANT because IL-6 inhibition may interfere with the normal immune response to new antigens [see Use in Specific Populations (8.1)].

5.3 Infusion Related Reactions and Hypersensitivity

SYLVANT may cause infusion related reactions and anaphylaxis. Approximately 945 patients have been treated with SYLVANT in clinical trials. Of these, one patient experienced an anaphylactic reaction. Data from 254 patients treated with SYLVANT monotherapy forms the basis of the safety evaluation of infusion related reactions. Infusion related reactions were reported in 5.1% of these patients. Two (0.8%) were Grade 3 or higher, and 1 (0.4%) was serious; none were fatal. Symptoms of infusion reactions consisted of back pain, chest pain or discomfort, nausea and vomiting, flushing, erythema, and palpitations.

In long-term treatment of MCD patients with siltuximab at the recommended dosage of 11 mg/kg every 3 weeks, infusion related reactions or hypersensitivity reactions occurred at a frequency of 6.3% (1.3% for severe reactions).

Stop the infusion of SYLVANT if the patient develops signs of anaphylaxis. Discontinue further therapy with SYLVANT.

Stop the infusion if the patient develops a mild to moderate infusion reaction. If the reaction resolves, the SYLVANT infusion may be restarted at a lower infusion rate. Consider medication with antihistamines, acetaminophen, and corticosteroids. Discontinue SYLVANT if the patient does not tolerate the infusion following these interventions [see Adverse Reactions (6)].

Administer SYLVANT in a setting that provides resuscitation equipment, medication, and personnel trained to provide resuscitation.

5.4 Gastrointestinal Perforation

Gastrointestinal (GI) perforation has been reported in clinical trials although not in MCD trials. Use with caution in patients who may be at increased risk for GI perforation. Promptly evaluate patients presenting with symptoms that may be associated or suggestive of GI perforation.

6 ADVERSE REACTIONS

The following clinically significant adverse reactions are also discussed in other sections of the labeling:

- Concurrent active severe infections [see Warnings and Precautions (5.1)]
- Infusion-related reactions and hypersensitivity [see Warnings and Precautions (5.3)]
- Gastrointestinal perforation [see Warnings and Precautions (5.4)]

6.1 Clinical Trials Experience

Because clinical trials are conducted under widely varying conditions, adverse reaction rates observed in the clinical trials of a drug cannot be directly compared to rates in the clinical trials of another drug and may not reflect the rates observed in clinical practice.

Study 1, in MCD, was an international, multicenter, randomized Phase 2 study of every 3 week infusions comparing SYLVANT and best supportive care (BSC) to placebo and BSC. There were 53 patients randomized to the SYLVANT arm at a dosage of 11 mg/kg and 26 patients randomized to the placebo arm. Of the 26 placebo-treated patients, 13 patients subsequently crossed-over to receive SYLVANT. The median age was 48 years (range 20 to 78), 66% male, 48% Asian, 39% White, 4% Black or African American, 7% other. The patients randomized to SYLVANT received a median of 19 infusions (range 1 to 50) compared to patients randomized to placebo who received a median of 8 infusions (range 2 to 32). To control for disparate exposure between arms, Table 3 reports the per patient incidence of adverse reactions that occurred during the first 8 infusions. Adverse reactions that occurred >3% in the SYLVANT arm are presented.

The most common adverse reactions (> 10% compared to placebo) during treatment with SYLVANT in the MCD clinical trial were rash, pruritus, upper respiratory tract infection, increased weight, and hyperuricemia.

Table 3: Per Patient Incidence of Common Adverse Reactions in Study 1 During Initial 8 Infusions
Body System/Adverse Reactions | SYLVANT+BSC [Best Supportive Care] n=53 |  | Placebo+BSC n=26
 | All Grades | Grades 3-4 | All Grades | Grades 3-4
Skin disorders
Rash (rash, rash generalized, rash maculo-papular, rash popular and rash pruritic) | 15 (28%) | 1 (2%) | 3 (12%) | 0
Pruritus | 15 (28%) | 0 | 2 (8%) | 0
Skin hyperpigmentation | 2 (4%) | 0 | 0 | 0
Eczema | 2 (4%) | 0 | 0 | 0
Psoriasis | 2 (4%) | 0 | 0 | 0
Dry skin | 2 (4%) | 0 | 0 | 0
Infections
Lower respiratory tract | 4 (8%) | 2 (4%) | 1 (4%) | 1 (4%)
Upper respiratory tract | 14 (26%) | 1 (2%) | 4 (15%) | 1 (4%)
Blood and lymphatic system disorders
Thrombocytopenia | 5 (9%) | 2 (4%) | 1 (4%) | 1 (4%)
General disorders
Edema (general and localized) | 14 (26%) | 4 (8%) | 7 (27%) | 0
Gastrointestinal disorders
Constipation | 4 (8%) | 0 | 1 (4%) | 0
Metabolism
Hypertriglyceridemia | 4 (8%) | 0 | 0 | 0
Hypercholesterolemia | 2 (4%) | 0 | 0 | 0
Hyperuricemia | 6 (11%) | 1 (2%) | 0 | 0
Respiratory, thoracic and mediastinal disorders
Oropharyngeal pain | 4 (8%) | 0 | 1 (4%) | 0
Renal and urinary disorders
Renal impairment | 4 (8%) | 0 | 0 | 0
Nervous system disorders
Headache | 4 (8%) | 0 | 1 (4%) | 0
Investigations
Weight increased | 10 (19%) | 1 (2%) | 0 | 0
Vascular disorders
Hypotension | 2 (4%) | 1 (2%) [Anaphylactic reaction] | 0 | 0

Study CNTO328MCD2002 (referred to as Study 2) (NCT01400503) was an open label, long term extension study of patients with MCD treated on prior trials. The median duration of siltuximab treatment was 5.52 years (range: 0.8 to 10.8 years); more than 50% of patients received siltuximab treatment for ≥5 years. The rate of serious or Grade ≥3 adverse events did not increase over time as a function of cumulative exposure.

Other important adverse reactions reported in MCD clinical studies, all of which were very common, were:

Infections and infestations: nasopharyngitis, urinary tract infection

Blood and lymphatic system disorders: neutropenia

Nervous system disorders: dizziness

Vascular disorders: hypertension

Gastrointestinal disorders: nausea, abdominal pain, vomiting, diarrhea, gastroesophageal reflux disease, mouth ulceration

6.2 Immunogenicity

Immunogenicity data are highly dependent on the sensitivity and specificity of the test methods used. Additionally, the observed incidence of a positive result in a test method may be influenced by several factors, including sample handling, timing of sample collection, drug interference, concomitant medication and the underlying disease. Therefore, comparison of the incidence of antibodies to SYLVANT with the incidence of antibodies to other products may be misleading. The clinical significance of anti-siltuximab antibodies following treatment with SYLVANT is not known.

The immunogenicity of siltuximab has been evaluated using antigen-bridging enzyme immunoassay (EIA) and electrochemiluminescence-based immunoassay (ECLIA) methods. A total of 432 patients across the clinical studies were evaluated at multiple time points for anti-therapeutic antibody (ATA) responses to siltuximab after treatment with SYLVANT. Following SYLVANT dosing, 0/243 (0%) patients tested positive for anti-siltuximab antibodies by EIA and 4/189 (2%) patients tested positive by ECLIA. Further immunogenicity analyses were conducted for all positive samples from the 4 patients with detectable anti-siltuximab antibodies. None of these patients had neutralizing antibodies.

7 DRUG INTERACTIONS

7.1 Cytochrome P450 Substrates

Cytochrome P450s in the liver are down regulated by infection and inflammation stimuli including cytokines such as IL-6. Inhibition of IL-6 signaling in patients treated with SYLVANT may restore CYP450 activities to higher levels leading to increased metabolism of drugs that are CYP450 substrates compared to metabolism prior to treatment with SYLVANT.

Upon initiation or discontinuation of SYLVANT, in patients being treated with CYP450 substrates with a narrow therapeutic index, perform therapeutic monitoring of effect (e.g., warfarin) or drug concentration (e.g., cyclosporine or theophylline) as needed and adjust dose. The effect of SYLVANT on CYP450 enzyme activity can persist for several weeks after stopping therapy. Exercise caution when SYLVANT is co-administered with CYP3A4 substrate drugs where a decrease in effectiveness would be undesirable (e.g., oral contraceptives, lovastatin, atorvastatin).

8 USE IN SPECIFIC POPULATIONS

8.1 Pregnancy

Risk-Summary

In an animal reproduction study, intravenous administration of a human antibody to IL-6 to pregnant monkeys from the onset of organogenesis through delivery caused functional impairment in pregnant animals and in the offspring. Siltuximab and the human antibody to IL-6 crossed the placenta in monkeys (see Data). The limited available information on SYLVANT use during pregnancy is not sufficient to inform a drug-associated risk of major birth defects or miscarriage. Infants born to pregnant women treated with SYLVANT may be at increased risk of infection (see Clinical Considerations). Advise pregnant women of the potential risk to a fetus.

The estimated background risk for the indicated population is unknown. All pregnancies have a background risk of birth defect, loss, or other adverse outcomes. In the U.S. general population, the estimated background risk of major birth defects is 2% to 4% and of miscarriage is 15% to 20% of clinically recognized pregnancies.

Clinical Considerations

Fetal/Neonatal adverse reactions

Monoclonal antibodies are transported across the placenta as pregnancy progresses, with the largest amount transferred during the third trimester. Infants born to pregnant women treated with SYLVANT may be at increased risk of infection. Consider the risks and benefits of administering live or live-attenuated vaccines to infants exposed to SYLVANT in utero [see Warnings and Precautions (5.2)].

Data

Animal Data

In an embryo-fetal development study in cynomolgus monkeys, pregnant animals received intravenous doses of siltuximab of 9.2 or 46 mg/kg/week during gestation days (GD) 20 to 118, which includes the period of organogenesis. Fetuses were evaluated on GD 140, approximately 25 days prior to the natural birth. Exposures at the low and high dose after the 25th administration were approximately 3 and 7 times, respectively, the human exposure based on AUC in patients with MCD at the recommended dose of 11 mg/kg every three weeks. No maternal or fetal structural abnormalities were observed. However, siltuximab crossed the placenta at both doses and when measured on GD 140, fetal serum concentrations of siltuximab were similar to maternal concentrations. In a combined embryofetal and pre- and post-natal development study in cynomolgus monkeys, pregnant animals received intravenous doses of 10 or 50 mg/kg/week of a human antibody to IL-6 from GD 20 to natural delivery (GD 167). The offspring were evaluated up to 7 months after birth for developmental effects. No maternal or infant structural abnormalities were observed; however, globulin levels were decreased in pregnant animals (GD 34 through lactation day 30) and in the offspring (lactation days 30-120) at both doses.

8.2 Lactation

Risk Summary

There are no data on the presence of siltuximab in human milk, the effects on the breastfed child, or the effects on milk production. However, low levels of the human antibody to IL-6 was present in the milk of lactating cynomolgus monkeys. When a drug is present in animal milk, it is likely that the drug will be present in human milk. Because of the potential for serious adverse reactions in the breastfed child including gastrointestinal perforations, advise patients that breastfeeding is not recommended during treatment with SYLVANT, and for 3 months after the last dose.

8.3 Females and Males of Reproductive Potential

Contraception

Females

SYLVANT may cause embryo-fetal harm when administered to pregnant women [see Use in Specific Populations (8.1)]. Advise female patients of reproductive potential to use effective contraception during treatment with SYLVANT and for 3 months after the last dose.

8.4 Pediatric Use

The safety and efficacy of SYLVANT have not been established in pediatric patients.

8.5 Geriatric Use

Of the patients treated with SYLVANT monotherapy in clinical studies 127 (35%) were 65 years and older. No overall differences in safety profile were observed between these patients and younger patients, and other reported clinical experience has not identified differences in the safety profile between the elderly and younger patients, but greater sensitivity of some older individuals cannot be ruled out. Clinical studies did not include sufficient numbers of patients aged 65 years and older to determine the effect of age on efficacy in MCD population.

8.6 Patients with Renal Impairment

Based on a population pharmacokinetic analysis using data from clinical trials in patients, no significant difference in siltuximab clearance was observed in patients with pre-existing renal impairment (creatinine clearance (CLCr) ≥ 15 mL/min) compared to patients with baseline normal renal function (CLCr ≥ 90 mL/min). No initial dosage adjustment is necessary for patients with CLCr ≥ 15 mL/min. The potential effect of end stage renal disease on siltuximab pharmacokinetics cannot be determined [see Clinical Pharmacology (12.3)].

8.7 Patients with Hepatic Impairment

Based on a population pharmacokinetic analysis using data from clinical trials in patients, no significant difference in siltuximab clearance was observed in patients with pre-existing mild to moderate hepatic impairment (Child-Pugh Class A and B, respectively) compared to patients with baseline normal hepatic function. No initial dosage adjustment is necessary for patients with mild to moderate hepatic impairment. Patients with baseline severe hepatic impairment (Child-Pugh Class C) were not included in clinical trials [see Clinical Pharmacology (12.3)].

11 DESCRIPTION

Siltuximab is a human-mouse chimeric monoclonal antibody that binds human interleukin-6 (IL-6) and is produced by Chinese hamster ovary cells.

SYLVANT (siltuximab) for injection is supplied as a sterile, white, preservative free, lyophilized powder in single-dose vials.

Each SYLVANT 100 mg single-dose vial contains 100 mg siltuximab, 3.7 mg L-histidine (from L-histidine and L-histidine monohydrochloride monohydrate), 0.8 mg polysorbate 80, and 169 mg sucrose.

Each SYLVANT 400 mg single-dose vial contains 400 mg siltuximab, 14.9 mg L-histidine (from L-histidine and L-histidine monohydrochloride monohydrate), 3.2 mg polysorbate 80, and 677 mg sucrose.

Following reconstitution with Sterile Water for Injection, USP (per section 2.2), the resulting pH is approximately 5.2. The resulting solution contains 20 mg/mL siltuximab to be administered by intravenous infusion following dilution [see Dosage and Administration (2.2)].

12 CLINICAL PHARMACOLOGY

12.1 Mechanism of Action

Siltuximab binds human IL-6 and prevents the binding of IL-6 to both soluble and membrane-bound IL-6 receptors. IL-6 has been shown to be involved in diverse normal physiologic processes such as induction of immunoglobulin secretion. Overproduction of IL-6 has been linked to systemic manifestations in patients with MCD.

12.2 Pharmacodynamics

Cardiac Electrophysiology: The effect of multiple doses of SYLVANT (15 mg/kg every 3 weeks for 4 cycles) on the QTc interval was evaluated in an open label, single arm study in 30 patients with Monoclonal Gammopathy of Undetermined Significance, Smoldering Multiple Myeloma, or Indolent Multiple Myeloma. No large changes in the mean QTc interval (i.e., > 20 ms) were detected in the study.

Measurement of IL-6 concentrations in serum or plasma during treatment should not be used as pharmacodynamic marker, as siltuximab-neutralized antibody-IL-6 complexes interfere with current immunological-based IL-6 quantification methods.

12.3 Pharmacokinetics

The pharmacokinetics of siltuximab were evaluated in patients with multicentric Castleman's disease and hematological and non-hematological malignancies. The serum siltuximab pharmacokinetics are adequately described by a linear two-compartment intravenous model with first-order elimination.

Distribution

Following SYLVANT administration (11 mg/kg, once every 3 weeks as 1-hour intravenous infusion) in patients with multicentric Castleman's disease, the maximum serum siltuximab concentration (Cmax) occurred close to the end of infusion. At steady state, the serum mean Cmax value for siltuximab is 332 mcg/mL (42% CV), and the serum mean predose trough value is 84 mcg/mL (78% CV).

With the once every 3 week dosing regimen, siltuximab steady state is achieved by the sixth infusion, and siltuximab accumulates approximately 1.7-fold relative to a single dose. Following multiple dosing, siltuximab showed approximately dose proportional pharmacokinetics over the dose range of 2.8 to 11 mg/kg.

Based on population pharmacokinetic analysis, the central volume of distribution in a male subject with body weight of 70 kg is 4.5 L (20% CV).

Elimination

Based on the population pharmacokinetic analysis, the clearance of siltuximab in patients is 0.23 L/day (51% CV). Based on population pharmacokinetic analysis (n=378), body weight was identified as the only statistically significant covariate for siltuximab clearance. Therefore, the body weight based dosing is appropriate.

The mean terminal half-life (t1/2) for siltuximab in patients after the first intravenous infusion of 11 mg/kg is 20.6 days (range: 14.2 to 29.7 days).

Specific Populations

Age and Gender

Based on population pharmacokinetic analysis, age [range: 18 to 85 years (n=378)] and gender [female (n=175), male (n=203)] do not affect exposure of siltuximab.

Renal Impairment

A population pharmacokinetic analysis (based on pre-existing renal function) was carried out with data from 377 patients enrolled in clinical trials, including 176 with normal renal function (CLCr ≥ 90 mL/min), 122 with mild renal impairment (CLCr 60 to <90 mL/min), 75 with moderate renal impairment (CLCr 30 to <60 mL/min), and 3 with severe renal impairment (CLCr 15 to 29 mL/min). The apparent clearance of siltuximab was similar in patients with pre-existing mild, moderate and severe renal impairment (CLCr 15 to <90 mL/min) compared to patients with normal renal function. The potential effect of end stage renal disease on siltuximab pharmacokinetics cannot be determined as clinical and pharmacokinetic data are available from only one patient.

Hepatic Impairment

A population pharmacokinetic analysis (based on pre-existing hepatic function) was carried out with data from 377 patients enrolled in clinical trials, including 302 with normal hepatic function, 72 with mild hepatic impairment (Child-Pugh A), and 3 with moderate hepatic impairment (Child-Pugh B). The apparent clearance of siltuximab was similar in patients with pre-existing mild and moderate hepatic impairment (Child-Pugh Class A and B) compared to patients with normal hepatic function. The potential effect of severe hepatic impairment on siltuximab pharmacokinetics cannot be determined as clinical and pharmacokinetic data are not available.

13 NONCLINICAL TOXICOLOGY

13.1 Carcinogenesis, Mutagenesis, Impairment of Fertility

No carcinogenicity or genotoxicity studies have been conducted with siltuximab.

Two fertility studies were conducted. In one study, drug-treated male mice were mated with untreated females and in the second study drug-treated female mice were mated with untreated males. A murine analog of siltuximab was administered subcutaneously at doses up to 100 mg/kg/week for a total of 7 doses in both studies. There was no effect on male or female fertility parameters. In addition, siltuximab did not produce any toxicity in the reproductive organs in cynomolgus monkeys in the 6-month repeat-dose toxicology study at doses up to 46 mg/kg (approximately 7 times) the systemic exposure in patients at the recommended dose.

14 CLINICAL STUDIES

Study 1

Study CNTO328MCD2001 (referred to as Study 1) (NCT01024036) was a Phase 2, multinational, randomized (2:1) double blind, placebo controlled study to evaluate the clinical efficacy and safety of SYLVANT for the treatment of patients with MCD. In this study 53 patients were randomized to Best Supportive Care (BSC) and SYLVANT at a dose of 11 mg/kg every 3 weeks and 26 patients were randomized to BSC and placebo. The median age was 48 years (range 20 to 78), 66% male, 48% Asian, 39% White, 4% Black or African American, 7% other. The histological subtype of MCD was similar in both treatment arms, with 33% hyaline vascular subtype, 23% plasmacytic subtype and 44% mixed subtype. Treatment was continued until treatment failure (defined as disease progression based on increase in symptoms, radiologic progression or deterioration in performance status) or unacceptable toxicity.

The major efficacy outcome of the study was durable tumor and symptomatic response, defined as tumor response (PR and CR based on modified International Working Group response criteria for malignant lymphoma) assessed by independent review and complete resolution or stabilization of MCD symptoms. Thirty-four MCD related signs and symptoms prospectively identified were collected and graded according to the NCI-CTCAE v 4, by investigators. A durable response was defined as tumor and symptomatic response that persisted for a minimum of 18 weeks without treatment failure. The durable tumor and symptomatic response in the SYLVANT arm was 34% compared to 0% in the placebo arm (95% CI: 11.1, 54.8; p=0.0012).

Other analyses included tumor response, time to treatment failure and an increase in hemoglobin of 1.5 g/dL or more, in patients who were anemic at time of study entry, at week 13. The results are summarized in Table 4.

Table 4: Efficacy Endpoints From Study 1
Efficacy Endpoint | SYLVANT n=53 | Placebo n=26 | p-value [Adjusted for corticosteroid use at randomization]
Durable tumor and symptomatic response (independent review) | 34% | 0 | 0.0012
Tumor response | 38% | 4% | <0.05
Median time to treatment failure (days) | NR [NR="Not Reached"] | 134 | <0.05
≥1.5 g/dL increase in hemoglobin | 61% (19/31) | 0% (0/11) | <0.05

A consistent treatment effect was confirmed on subgroup analysis for all parameters evaluated with the exception of the hyaline vascular histological subtype. There were no patients with hyaline vascular histology who demonstrated a durable tumor and symptomatic response. However, activity was suggested in this subtype based on change in hemoglobin and median time to treatment failure.

At the time of the analysis, overall survival data were not mature. One year survival rate was 100% in the SYLVANT arm and 92% in the placebo arm.

16 HOW SUPPLIED/STORAGE AND HANDLING

16.1 How Supplied

SYLVANT (siltuximab) for injection is supplied as a sterile, white, preservative free, lyophilized powder in single-dose vials.

Each SYLVANT vial is individually packaged in a carton:

- NDC: 73090-420-01 contains one 100 mg vial
- NDC: 73090-421-01 contains one 400 mg vial

16.2 Storage and Stability

SYLVANT must be refrigerated at 2°C to 8°C (36°F to 46°F) in the original carton to protect from light. Do not freeze. Do not use SYLVANT beyond the expiration date (EXP) located on the carton and the vial.

17 PATIENT COUNSELING INFORMATION

Advise the patient to read the FDA-approved patient labeling (Patient Information).

Instruct the patient of the risks of SYLVANT treatment.

Infections

Inform patients that SYLVANT may lower their resistance to infections. Instruct the patient of the importance of contacting their doctor immediately when symptoms suggesting infection appear in order to assure rapid evaluation and appropriate treatment.

Vaccination

Inform the patient that they should discuss the recommended vaccinations prior to treatment with SYLVANT. Advise females with infants exposed to SYLVANT in utero to inform the pediatrician of the exposure [see Use in Specific Populations (8.1)].

Allergic Reactions

Advise patients to seek immediate medical attention if they experience any symptoms of serious allergic reactions during the infusion. Signs include: difficulty breathing, chest tightness, wheezing, severe dizziness or light-headedness, swelling of the lips or skin rash.

Pregnancy

Advise patients of childbearing potential to avoid pregnancy and to use contraception during treatment and for 3 months after the last dose of SYLVANT.

Lactation

Advise females not to breastfeed during treatment with SYLVANT and for 3 months after the final dose [see Use in Specific Populations (8.2)].

Manufactured by:
Recordati Rare Diseases Inc.
Bridgewater, NJ 08807 U.S.A.

U.S. License: 1899

PATIENT INFORMATION
SYLVANT® (Sil-vant)
(siltuximab) for injection

What is SYLVANT?

SYLVANT is a prescription medicine used to treat people with multicentric Castleman's disease (MCD) who do not have human immunodeficiency virus (HIV) and human herpesvirus-8 (HHV-8) infection.

It is not known if SYLVANT is safe and effective in children.

Who should not receive SYLVANT?

Do not receive SYLVANT if you have had a severe allergic reaction to siltuximab or any of the ingredients in SYLVANT.

See the end of this leaflet for a complete list of ingredients in SYLVANT.

Before you receive SYLVANT, tell your healthcare provider about all of your medical conditions, including if you:

- have an infection. You should not receive SYLVANT if you have a severe infection.
- have had a recent vaccination or are scheduled to receive any vaccinations. You should not receive a live vaccine during your treatment with SYLVANT.
- have or have had any stomach or bowel (intestine) problems, such as diverticulitis or ulcers. Tell your healthcare provider if you have pain in your stomach area.
- are pregnant or plan to become pregnant. It is not known if SYLVANT will harm your unborn baby. You should not become pregnant while receiving treatment with SYLVANT. Females who are able to become pregnant should use effective birth control during treatment with SYLVANT and for 3 months after stopping treatment.
- are breastfeeding or plan to breastfeed. It is not known if SYLVANT passes into your breast milk. You and your healthcare provider should decide if you will take SYLVANT or breastfeed. You should not do both.

Tell your healthcare provider about all the medicines you take, including prescription and over-the-counter medicines, vitamins, and herbal supplements.

How will I receive SYLVANT?

- SYLVANT is given by an intravenous (IV) infusion into a vein over 1 hour.
- SYLVANT is given every 3 weeks.

What are the possible side effects of SYLVANT?

SYLVANT may cause serious side effects, including:

- Infections. SYLVANT may lower your ability to fight infections. Tell your healthcare provider right away if you have any signs or symptoms of an infection during treatment with SYLVANT.
- Infusion and allergic reactions. If you have an infusion or allergic reaction while receiving SYLVANT, your healthcare provider will stop your infusion and treat your reaction. If you have a severe infusion or allergic reaction, your healthcare provider may stop your treatment completely. Tell your healthcare provider or get medical help right away if you have any of these symptoms during or after your infusion of SYLVANT:

- back pain
- chest pain or tightness
- nausea and vomiting
- flushing
- redness
- irregular heart beat (palpitations)

- trouble breathing
- wheezing
- dizziness or light-headedness
- swelling of the lips
- skin rash
- headache
- itching

The most common side effects of SYLVANT include: rash, itching, upper respiratory tract infection, swelling, weight gain, and increased blood level of uric acid.

These are not all the possible side effects of SYLVANT. Call your doctor for medical advice about side effects. You may report side effects to FDA at 1-800-FDA-1088.

General information about the safe and effective use of SYLVANT

Medicines are sometimes prescribed for purposes other than those listed in a Patient Information leaflet. You can ask your healthcare provider or pharmacist for information about SYLVANT that is written for health professionals.

What are the ingredients in SYLVANT?

Active ingredient: siltuximab

Inactive ingredients: L-histidine and L-histidine monohydrochloride monohydrate, polysorbate 80, and sucrose

Manufactured by: Recordati Rare Diseases Inc.
Bridgewater, NJ 08807 U.S.A.
U.S. License 1899
For more information, call 1-888-575-8344 or email medinfo@recordatirarediseases.com.

This Patient Information has been approved by the U.S. Food and Drug Administration.

Revised: 06/2024

PRINCIPAL DISPLAY PANEL - 100 mg Vial Box

NDC 73090-420-01

Single-Dose Vial
Discard Unused Portion

sylvant®
(siltuximab)
For Injection

100 mg

For Intravenous
Infusion Only

Reconstitution: Reconstitute with
5.2 mL Sterile Water for Injection, USP.
Dilution: Must be further diluted with
5% Dextrose Injection, USP.

RECORDATI
RARE DISEASES

Rx Only

PRINCIPAL DISPLAY PANEL - 400 mg Vial Box

NDC 73090-421-01

Single-Dose Vial
Discard Unused Portion

sylvant®
(siltuximab)
For Injection

400 mg

For Intravenous Infusion Only

Reconstitution: Reconstitute with
20 mL Sterile Water for
Injection, USP.
Dilution: Must be further diluted with
5% Dextrose Injection, USP.

RECORDATI
RARE DISEASES
Rx Only